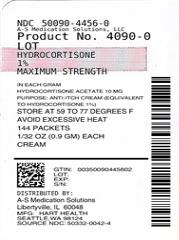 DRUG LABEL: HYDROCORTISONE
NDC: 50090-4456 | Form: CREAM
Manufacturer: A-S Medication Solutions
Category: otc | Type: HUMAN OTC DRUG LABEL
Date: 20191014

ACTIVE INGREDIENTS: HYDROCORTISONE ACETATE 10 mg/1 g
INACTIVE INGREDIENTS: CETYL ALCOHOL; CITRIC ACID ACETATE; DIAZOLIDINYL UREA; EDETATE DISODIUM; GLYCERIN; GLYCERYL MONOSTEARATE; METHYLPARABEN; MINERAL OIL; PROPYLENE GLYCOL; PROPYLPARABEN; WATER; STEARIC ACID; TROLAMINE

HYDROCORTISONE CREAM

Active Ingredient (in each gram): Hydrocortisone Acetate 10mg (equivalent to Hydrocortisone 1%)

Purpose: anti-itch cream

WARNINGS

Warnings: For external use only. Do not get in eyes

Allergy alert: A severe allergic reaction to insect bites or stings may require life support measures. In such cases, immediately clal 911 or your local emergency provider.

Do not use:

- in the eyes or over large portions of the body
- for the treatment of diaper rash
- with any other hydrocortisone product

Stop use and ask a doctor if:

- condition worsens
- condition lasts for more than 7 days
- symptoms clear up and occur again within a few days

Keep out of reach of children. If swallowed get medical help or contact a Poison Control Center right away. 1-800-222-1222

Directions:

Adults and children 12 years of age and over: apply topically to the area 3 to 4 times daily.

Children under 12 years of age: do not use, ask a doctor

INACTIVE INGREDIENT

Inactive Ingredients: Cetyl Alcohol, Citric Acid, Diazolidinyl Urea, Edetate Disodium, Glycerin, Glyceryl Monostearate, Methylparaben, Mineral Oil, Polyethylene Glycol, Propylene Glycol, Propylparaben, Purified Water, Stearic Acid, Trolamine

HOW SUPPLIED

Product: 50090-4456

NDC: 50090-4456-0 .9 g in a PACKET / 10 in a BOX, UNIT-DOSE